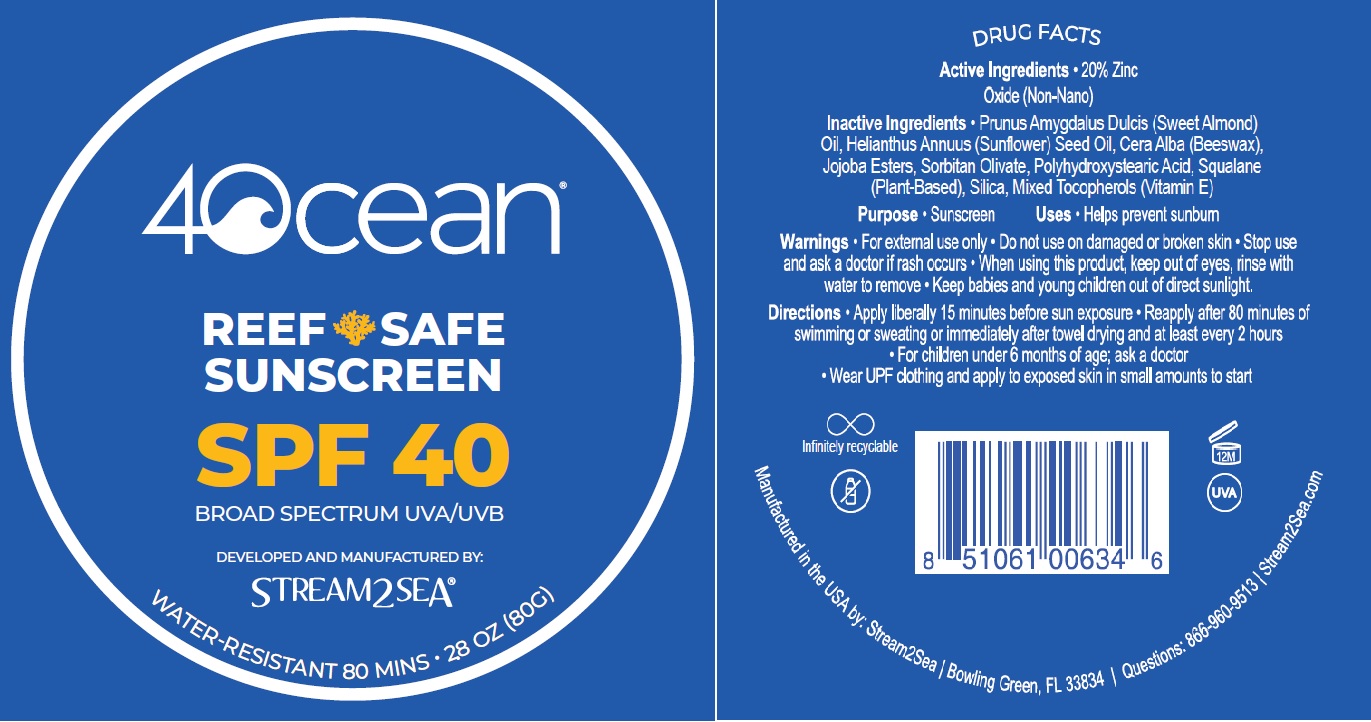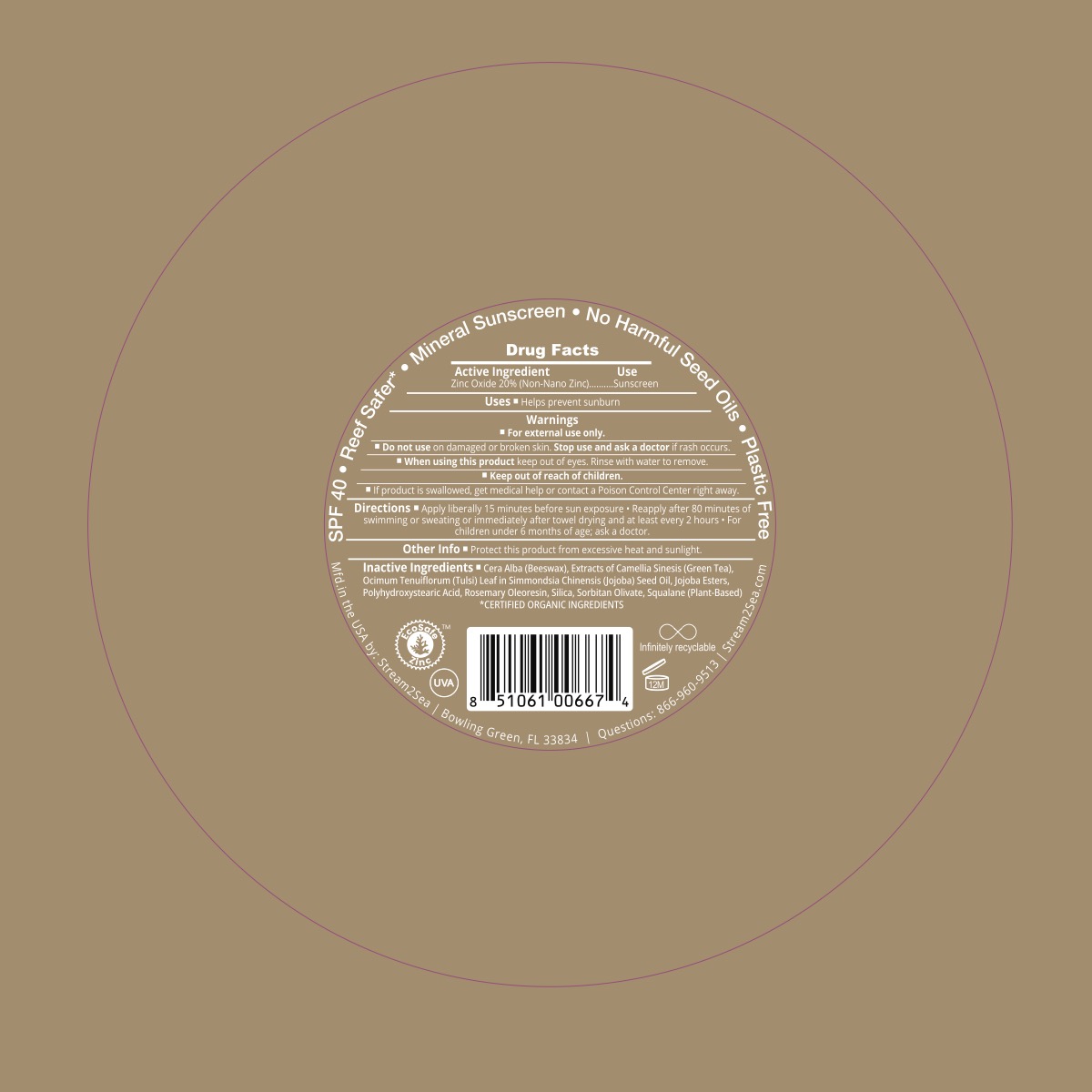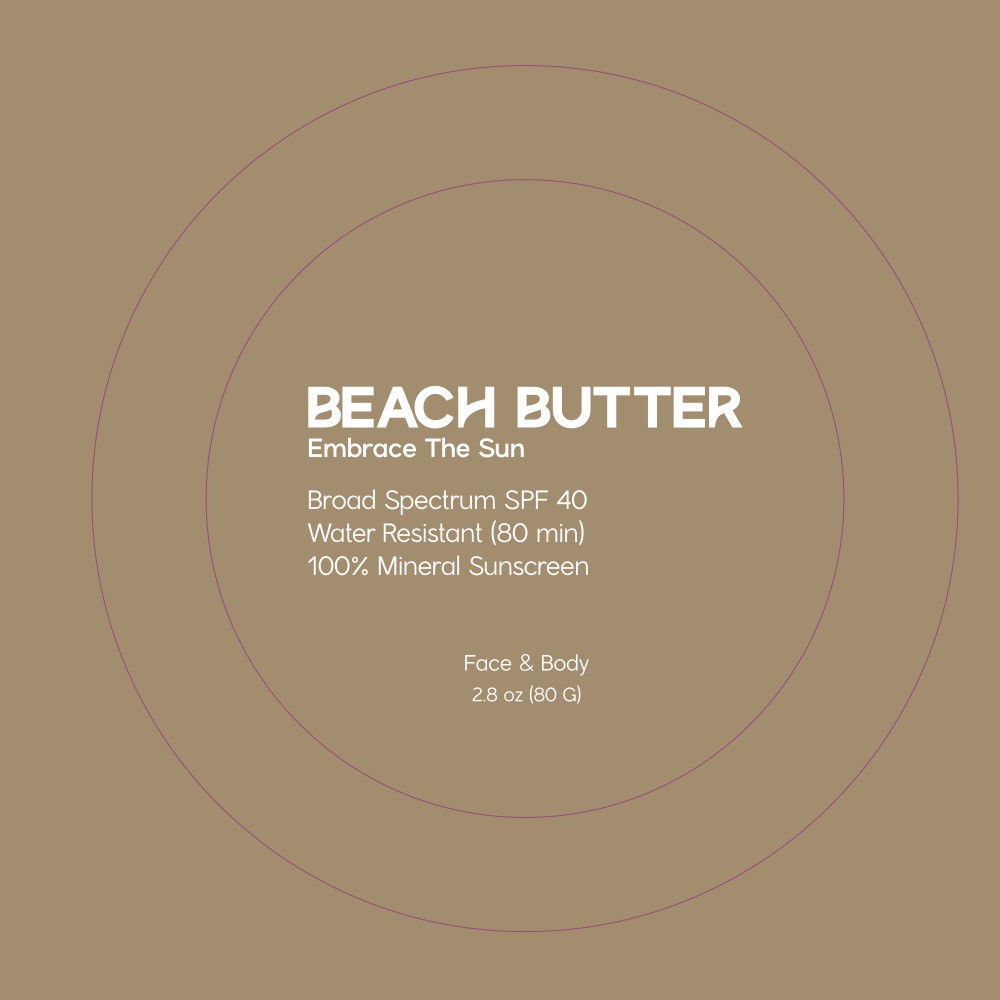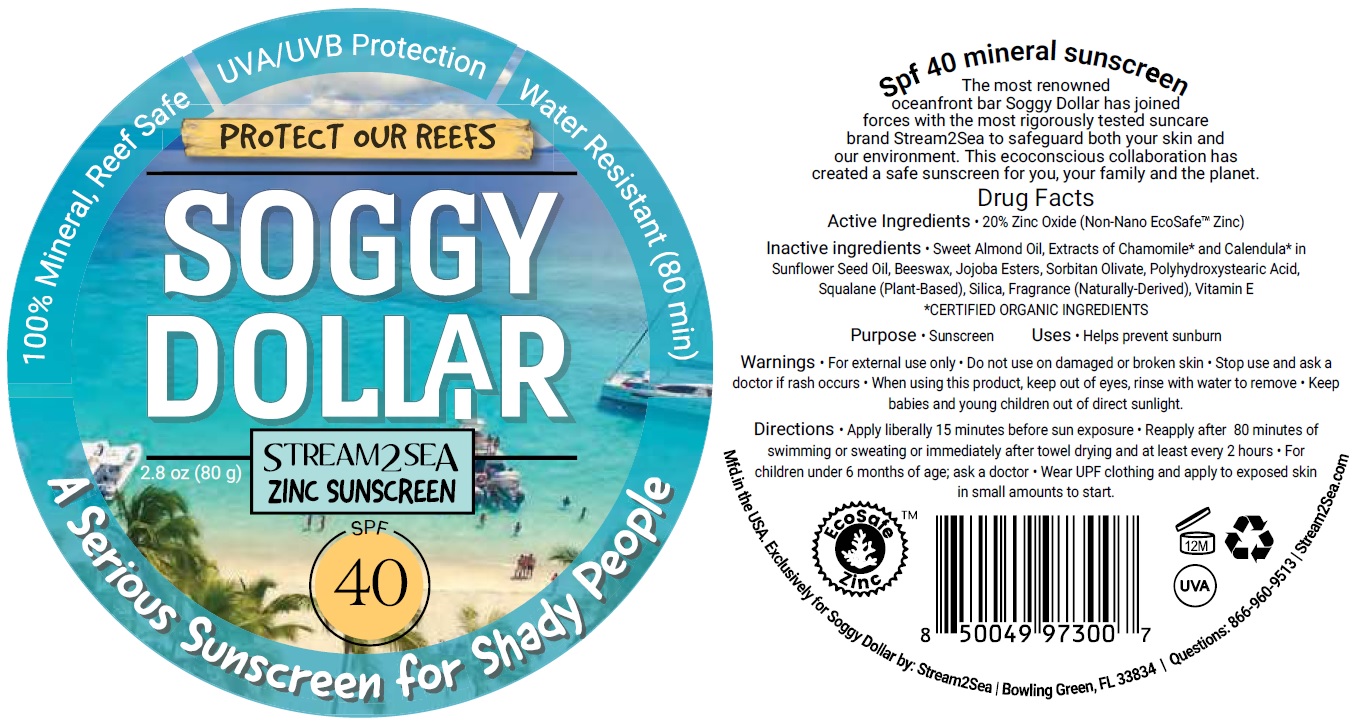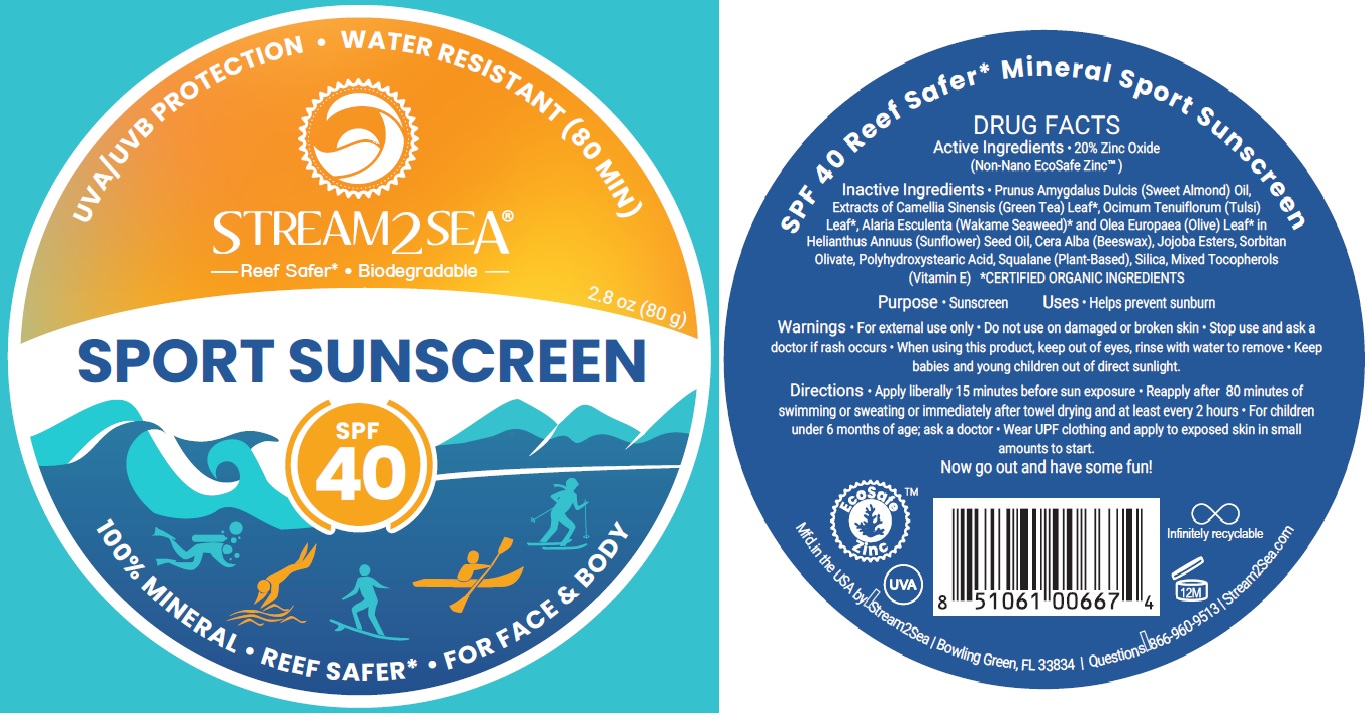 DRUG LABEL: 4ocean REEF SAFE SUNSCREEN SPF 40
NDC: 69555-040 | Form: CREAM
Manufacturer: Stream2Sea, LLC
Category: otc | Type: HUMAN OTC DRUG LABEL
Date: 20250516

ACTIVE INGREDIENTS: ZINC OXIDE 0.2 g/80 g
INACTIVE INGREDIENTS: TOCOPHEROL; ALMOND OIL; SUNFLOWER OIL; YELLOW WAX; SORBITAN OLIVATE; JOJOBA OIL; POLYHYDROXYSTEARIC ACID (2300 MW); SQUALANE; SILICON DIOXIDE

DRUG FACTS

Products Name | Active Ingredients
4OCEAN REEF SAFE SUNSCREEN SPF 40 | 20% Zinc Oxide (Non-Nano)
SPORT SUNSCREEN SPF 40 | 20% Zinc Oxide(Non-Nano EcoSafe Zinc™)
SOGGY DOLLAR ZINC SUNSCREEN SPF 40 | 20% Zinc Oxide (Non-Nano EcoSafeTM Zinc)

Purpose

- Sunscreen

Uses

- Helps prevent sunburn

Warnings

- For external use only.
- Do not use on damaged or broken skin.
- Stop use and ask a doctor if rash occurs.
- When using this product, keep out of eyes, rinse with water to remove.
- Keep babies and young children out of direct sunlight.

Directions

- Apply liberally 15 minutes before sun exposure.
- Reapply after 80 minutes of swimming or sweating or immediately after towel drying and at least every 2 hours.
- For children under 6 months of age; ask a doctor.
- Wear UPF clothing and apply to exposed skin in small amounts to start.

Inactive Ingredients

4OCEAN REEF SAFE SUNSCREEN SPF 40

- Prunus Amygdalus Dulcis (Sweet Almond) Oil, Helianthus Annuus (Sunflower) Seed Oil, Cera Alba (Beeswax), Jojoba Esters, Sorbitan Olivate, Polyhydroxystearic Acid, Squalane (Plant-Based), Silica, Mixed Tocopherols (Vitamin E).

SPORT SUNSCREEN SPF 40

- Prunus Amygdalus Dulcis (Sweet Almond) Oil, Extracts of Camellia Sinensis (Green Tea) Leaf*, Ocimum Tenuiflorum (Tulsi)Leaf*, Alaria Esculenta (Wakame Seaweed)* and Olea Europaea (Olive) Leaf* in Helianthus Annuus (Sunflower) Seed Oil, Cera Alba (Beeswax), Jojoba Esters, Sorbitan Olivate, Polyhydroxystearic Acid, Squalane (Plant-Based), Silica, Mixed Tocopherols (Vitamin E)*CERTIFIED ORGANIC INGREDIENTS.

SOGGY DOLLAR ZINC SUNSCREEN SPF 40

- Sweet Almond Oil, Extracts of Chamomile* and Calendula* in Sunflower Seed Oil, Beeswax, Jojoba Esters, Sorbitan Olivate, Polyhydroxystearic Acid, Squalane (Plant-Based), Silica, Fragrance (Naturally-Derived), Vitamin E *CERTIFIED ORGANIC INGREDIENTS.

Other Information for SOGGY DOLLAR ZINC SUNSCREEN SPF 40

The most renowned oceanfront bar Soggy Dollar has joined forces with the most rigorously tested suncare brand Stream2Sea to safeguard both your skin and our environment. This ecoconscious collaboration has created a safe sunscreen for you, your family and the planet.

Manufactured in the USA by: Stream2Sea, LLC

Bowling Green, FL 33834

Questions: 866-960-9513

Stream2Sea.com

PACKAGE LABEL.PRINCIPAL DISPLAY PANEL

4Ocean Reef Safe Sunscreen SPF 40 - Jar Label

Sport Sunscreen SPF 40 Jar Label

Soggy Dollar Sinc Sunscreen SPF 40 Jar Label